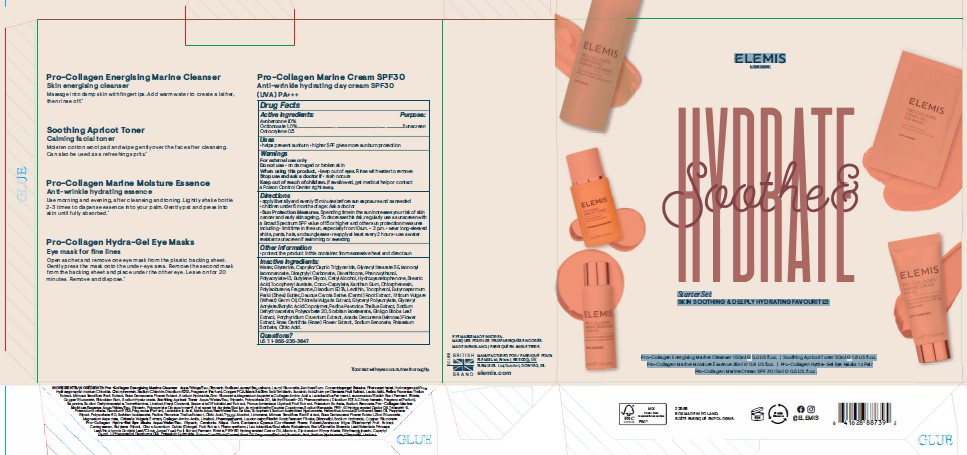 DRUG LABEL: Soothe and Hydrate Starter Set
NDC: 69378-009 | Form: KIT | Route: TOPICAL
Manufacturer: Acheson & Acheson Ltd.
Category: otc | Type: HUMAN OTC DRUG LABEL
Date: 20221214

ACTIVE INGREDIENTS: OCTOCRYLENE 5 mg/1 g; OCTINOXATE 10 mg/1 g; AVOBENZONE 10 mg/1 g
INACTIVE INGREDIENTS: POLYSORBATE 20; SORBITAN ISOSTEARATE; GINKGO; ACACIA DECURRENS FLOWER; PORPHYRIDIUM PURPUREUM; PHENOXYETHANOL; CETYL ALCOHOL; POLYISOBUTYLENE (1000 MW); XANTHAN GUM; CHLORPHENESIN; LECITHIN, SOYBEAN; CHLORELLA VULGARIS; PADINA PAVONICA; DIMETHICONE; BUTYLENE GLYCOL; HYDROXYACETOPHENONE; STEARIC ACID; .ALPHA.-TOCOPHEROL ACETATE; COCO-CAPRYLATE; SHEA BUTTER; DICAPRYLYL CARBONATE; ROSA CENTIFOLIA FLOWER; SODIUM BENZOATE; POTASSIUM SORBATE; GLYCERIN; WATER; MEDIUM-CHAIN TRIGLYCERIDES; GLYCERYL STEARATE SE; ISONONYL ISONONANOATE; EDETATE DISODIUM ANHYDROUS; TOCOPHEROL; CARROT; WHEAT GERM OIL; CITRIC ACID MONOHYDRATE; SODIUM DEHYDROACETATE

Soothe & Hydrate Starter Set

Questions?
UST: 1-855-235-3647

Inactive Ingredients

Water, Glycerine. Caprylic/Capric Triglyceride, Glyceryl StearateS E. lsononyl
lsononanoate. Dicaprylyt Carbonate, Dimethicone, Phenoxythanol,
Polyacrylate-13. Butylene Glycol. Cetyl Alcohol. Hydroxyacetophenone, Stearic
Acid, Tocopheryl Acetate, Coco-Caprylate. Xanthan Gum, Chlorphenesin,
Polyisobutene, Fragrance, Disodium EDTA, Lecithin, Tocopherol, Butyrospermum
Parkii (Shea) Butter, Daucus Carota Sativa (Carrot) Root Extract. Triticum Vulgare
(Wheat) Germ Oil, Chiarella Vulgaris Extract, Glyceryl Polyacrylate, Glyceryl
Acrylate/Acrylic Acid Copolymer, Padina Pavonica Thallus Extract, Sodium
Dehydroacetate, Polysorbate 20, Sorbitan lsostearate, Ginkgo Biloba Leaf
Extract. Porphyridium Cruentum Extract. Acacia Decurrens (Mimosa) Flower
Extract. Rosa Centifola (Rose) Flower Extract. Sodium Benzoate. Potassium
Sorbate, Citric Acid.

Other information

• protect the product in this container from excessive heat and direct sun

Directions

• apply liberally and evenly 15 minutes before sun exposure and as needed
• children under 6 months of age: Ask a doctor
• Sun Protection Measures.S pending time in the sun increases your risk of skin
cancer and early skin ageing, To decrease this risk, regularly use a sunscreen with
a Broad SpectrumS PF value of 15 or higher and other sun protection measures
including· limit time in the sun, especially from 1 0a.m. - 2 p.m. • wear long-sleeved
shirts. pants. hats. and sunglasses• reapply at least every 2 hours• use a water
resistant sunscreen if swimming or sweating

Warnings

For external use only
Do not use• on damaged or broken skin
When using this product, • keep out of eyes. Rinse with water to remove
Stop use and ask a doctor if• rash occurs
Keep oU1 of reach of children. If swallowed, get medical help or contact
a Poison Control Center right away.

Uses

helps prevent sunburn• higher SPF gives more sunburn protection

Purpose

Sunscreen

Active Ingredients

:
Avobenzone 1.0%
Octionoxate 1.0%
Octocrylene 0.5

PACKAGE LABEL

ELEMIS

LONDON

Soothe & Hydrate
Starter Set
SKIN SOOTHING & DEEPLY HYDRATING FAVOURITES
Pro-Collagen Energising Marine Cleanser 150ml e 5.0 US fl.oz. I Soothing Apricot Toner 50ml e 1.6 US fl.oz.
Pro-Collagen Marine Moisture Essence 28ml e 0.9 US fl.oz. I Pro-Collagen Hydra-Gel Eye Masks 1 x Pair
Pro-CollagenMarine Cream SPF 30 15ml e 0.5 US. fl.oz.